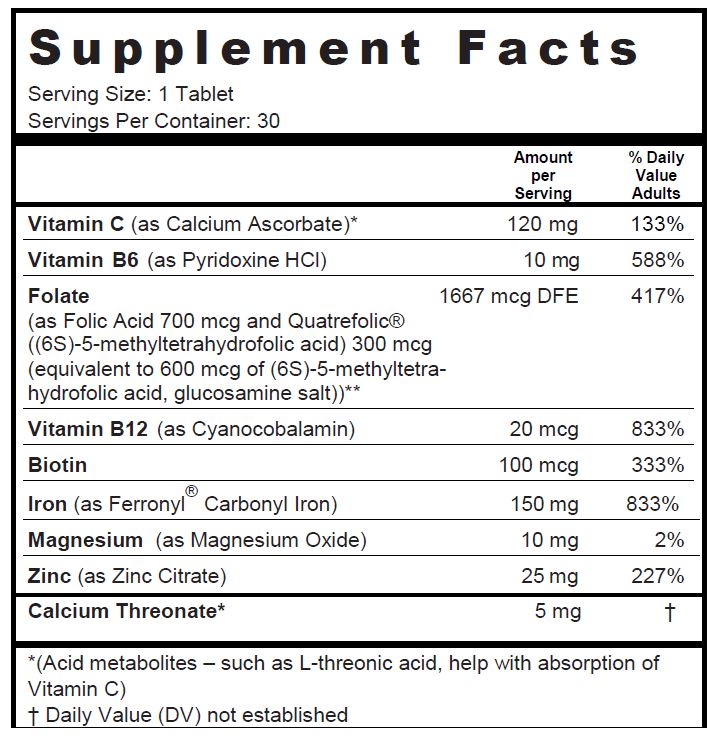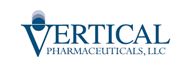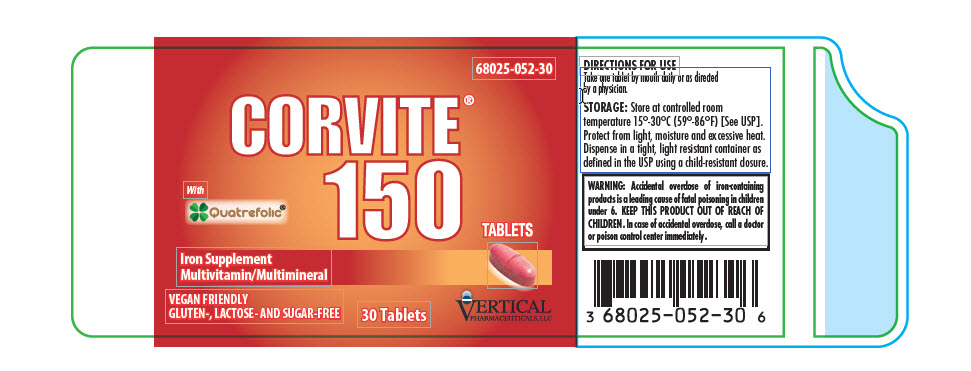 DRUG LABEL: Corvite 150
NDC: 68025-052 | Form: TABLET, COATED
Manufacturer: Vertical Pharmaceuticals, LLC
Category: other | Type: DIETARY SUPPLEMENT
Date: 20220107

ACTIVE INGREDIENTS: CALCIUM ASCORBATE 120 mg/1 1; CALCIUM THREONATE 5 mg/1 1; PYRIDOXINE HYDROCHLORIDE 10 mg/1 1; BIOTIN 100 ug/1 1; CYANOCOBALAMIN 20 ug/1 1; FOLIC ACID 700 ug/1 1; 5-METHYLTETRAHYDROFOLIC ACID 300 ug/1 1; IRON PENTACARBONYL 150 mg/1 1; MAGNESIUM OXIDE 10 mg/1 1; ZINC CITRATE 25 mg/1 1
INACTIVE INGREDIENTS: CELLULOSE, MICROCRYSTALLINE; STARCH, CORN; CALCIUM PHOSPHATE, DIBASIC, ANHYDROUS; HYPROMELLOSES; POLYVINYL ALCOHOL, UNSPECIFIED; FD&C RED NO. 40; ALUMINUM OXIDE; POLYETHYLENE GLYCOL, UNSPECIFIED; TALC; TITANIUM DIOXIDE; CROSCARMELLOSE SODIUM; STEARIC ACID; MAGNESIUM STEARATE

CORVITE® 150

SUPPLEMENT FACTS

Other Ingredients: Microcrystalline Cellulose, Pregelatinized Starch, di-Calcium Phosphate, Red Color Coating (Hydroxypropylmethyl Cellulose, Polyvinyl Alcohol, FD&C Red #40 Lake, Polyethylene Glycol, Talc, Titanium Dioxide), Croscarmellose Sodium, Stearic Acid, Magnesium Stearate

VEGAN FRIENDLY

GLUTEN-, LACTOSE- AND SUGAR-FREE

CORVITE®150 is a prescription hematinic multivitamin/multimineral dietary supplement used to improve the nutritional status of patients with iron deficiency.

Other Ingredients

Microcrystalline Cellulose, Pregelatinized Starch, di-Calcium Phosphate, Red Color Coating (Hydroxypropylmethyl Cellulose, Polyvinyl Alcohol, FD&C Red #40 Lake, Polyethylene Glycol, Talc, Titanium Dioxide), Croscarmellose Sodium, Stearic Acid, Magnesium Stearate.

Sugar, Lactose and Gluten Free

Vegan Safe

CONTRAINDICATIONS

CORVITE®150 should not be used by patients with a known hypersensitivity to any of the listed ingredients. All iron compounds are contraindicated in patients with hemochromatosis, hemosiderosis, or hemolytica anemias.

WARNINGS

WARNING: Accidental overdose of iron-containing products is a leading cause of fatal poisoning in children under 6. KEEP THIS PRODUCT OUT OF REACH OF CHILDREN. In case of accidental overdose, call a doctor or poison control center immediately.

PRECAUTIONS

Do not exceed recommended dose. The type of anemia and the underlying cause or causes should be determined before starting therapy with CORVITE®150. Since the anemia may be a result of a systemic disturbance, such as recurrent blood loss, the underlying cause or causes should be corrected, if possible.

Folic Acid: Folic acid alone is an improper therapy in the treatment of pernicious anemia and other megaloblastic anemias where vitamin B12 is deficient. Folic acid in doses above 0.1 mg daily may obscure pernicious anemia in that hematologic remission can occur while neurologic manifestations remain progressive. Allergic sensitization has been reported following both oral and parenteral administration of folic acid.

The patient’s medical conditions and consumption of other drugs, herbs, and/or supplements should be considered.

Pediatric Use: Safety and effectiveness in pediatric populations have not been established.

Geriatric Use: Safety and effectiveness in elderly populations have not been established.

Biotin levels higher than the recommended daily allowance may cause interference with some laboratory tests, including cardiovascular diagnostic tests (e.g. troponin) and hormone tests, and may lead to incorrect test results. Tell your healthcare provider about all prescription and over-the-counter medicines, vitamins, and dietary supplements that you take, including biotin.

DRUG INTERACTIONS

CORVITE® 150 is not recommended for and should not be given to patients receiving levodopa because the action of levodopa is antagonized by pyridoxine. There is a possibility of increased bleeding due to pyridoxine interaction with anticoagulants (e.g., Aspirin, Heparin, Clopidogrel).

ADVERSE REACTIONS

Adverse reactions with iron therapy may include constipation, diarrhea, nausea, vomiting, dark stools and abdominal pain. Adverse reactions with iron therapy are usually transient.

OVERDOSAGE

The clinical course of acute iron overdosage can be variable. Initial symptoms may include abdominal pain, nausea, vomiting, diarrhea, tarry stools, melena, hematemesis, hypotension, tachycardia, metabolic acidosis, hyperglycemia, dehydration, drowsiness, pallor, cyanosis, lassitude, seizures, shock and coma.

DESCRIPTION

CORVITE®150 is a red, oval shaped tablet imprinted with “VP052” on one side and bisected on the other side.

DIRECTIONS FOR USE

Take one tablet by mouth daily or as directed by a physician.

HOW SUPPLIED

CORVITE®150 is available in bottles of 30 tablets.

Product Code: 68025-052-30

STORAGE

Store at controlled room temperature 15°-30°C (59°-86°F) [See USP]. Protect from light, moisture and excessive heat. Dispense in a tight, light resistant container as defined in the USP using a child-resistant closure.

HEALTH CLAIM

KEEP THIS PRODUCT OUT OF REACH OF CHILDREN.

**Quatrefolic® is a registered trademark of Gnosis, SpA. U.S. Patent No. 7,947,662.

For use on the order of a healthcare practitioner

Call your doctor about side effects. To report side effects, call Vertical Pharmaceuticals at 1-770-509-4500 or FDA at 1-800-FDA-1088 or www.fda.gov/medwatch.

PLR-CORV150-00001-1 Rev. 12/2021

Distributed by:

Vertical Pharmaceuticals, LLC
Alpharetta, GA 30005
www.verticalpharma.com

PRINCIPAL DISPLAY PANEL - 30 Tablet Bottle Label

68025-052-30

CORVITE®150 TABLETS

Iron Supplement
Multivitamin/Multimineral

Vegan Friendly

GLUTEN, LACTOSE, AND SUGAR FREE

30 Tablets

VERTICAL PHARMACEUTICALS, LLC